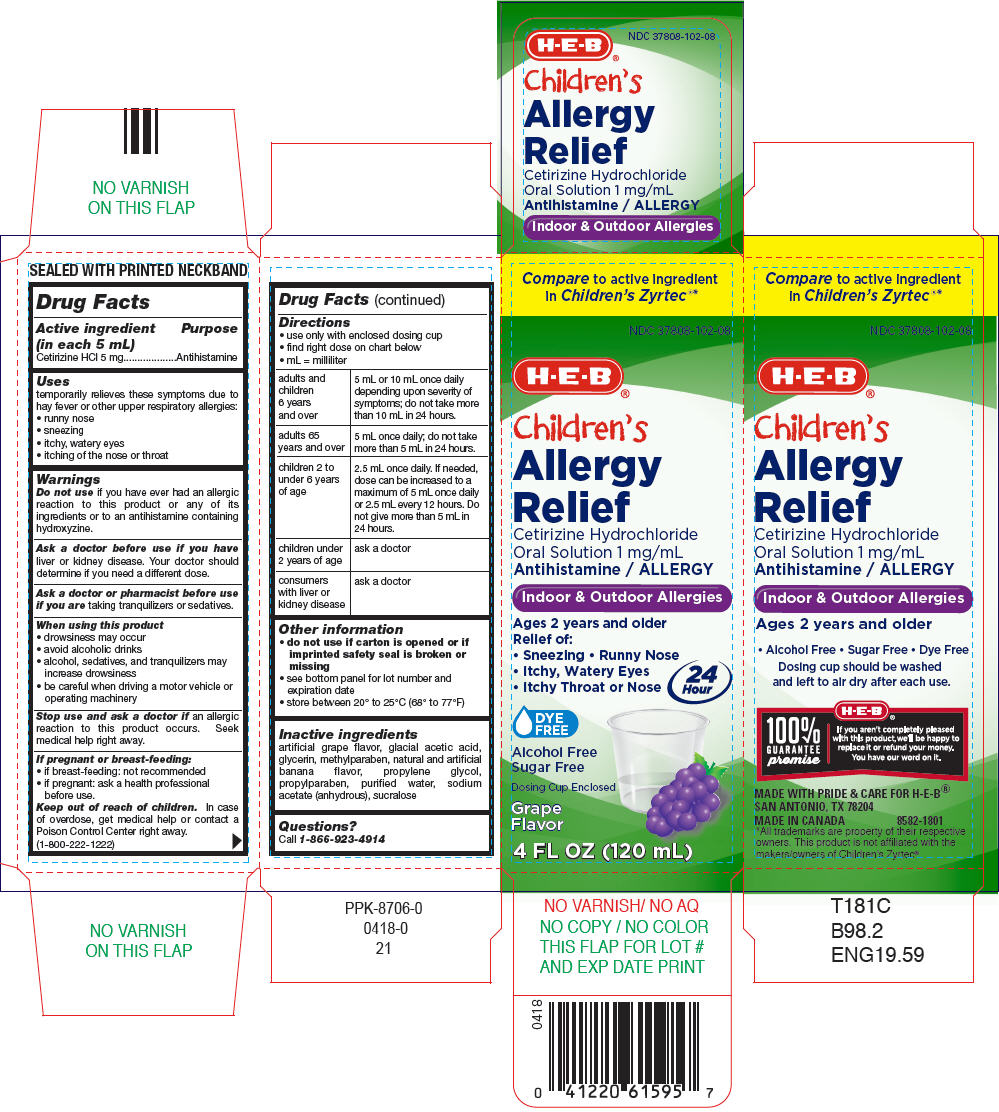 DRUG LABEL: HEB 

NDC: 37808-102 | Form: SOLUTION
Manufacturer: H E B
Category: otc | Type: HUMAN OTC DRUG LABEL
Date: 20251125

ACTIVE INGREDIENTS: CETIRIZINE HYDROCHLORIDE 5 mg/5 mL
INACTIVE INGREDIENTS: ACETIC ACID; GLYCERIN; METHYLPARABEN; PROPYLENE GLYCOL; PROPYLPARABEN; WATER; SODIUM ACETATE ANHYDROUS; SUCRALOSE

HEB®
Allergy Relief

Drug Facts

Active ingredient (in each 5 mL)

Cetirizine HCl 5 mg

Purpose

Antihistamine

Uses

temporarily relieves these symptoms due to hay fever or other upper respiratory allergies:

- runny nose
- sneezing
- itchy, watery eyes
- itching of the nose or throat

Warnings

DO NOT USE

Do not useif you have ever had an allergic reaction to this product or any of its ingredients or to an antihistamine containing hydroxyzine.

Ask a doctor before use if you haveliver or kidney disease. Your doctor should determine if you need a different dose.

Ask a doctor or pharmacist before use if you aretaking tranquilizers or sedatives.

When using this product

- drowsiness may occur
- avoid alcoholic drinks
- alcohol, sedatives, and tranquilizers may increase drowsiness
- be careful when driving a motor vehicle or operating machinery

Stop use and ask a doctor ifan allergic reaction to this product occurs. Seek medical help right away.

If pregnant or breast-feeding:

- if breast-feeding: not recommended
- if pregnant: ask a health professional before use.

Keep out of reach of children.In case of overdose, get medical help or contact a Poison Control Center right away. (1-800-222-1222)

Directions

- use only with enclosed dosing cup
- find right dose on chart below
- mL = milliliter

adults and children 6 years and over | 5 mL or 10 mL once daily depending upon severity of symptoms; do not take more than 10 mL in 24 hours.
adults 65 years and over | 5 mL once daily; do not take more than 5 mL in 24 hours.
children 2 to under 6 years of age | 2.5 mL once daily. If needed, dose can be increased to a maximum of 5 mL once daily or 2.5 mL every 12 hours. Do not give more than 5 mL in 24 hours.
children under 2 years of age | ask a doctor
consumers with liver or kidney disease | ask a doctor

Other information

- do not use if carton is opened or if imprinted safety seal is broken or missing
- see bottom panel for lot number and expiration date
- store between 20° to 25°C (68° to 77°F)

Inactive ingredients

artificial grape flavor, glacial acetic acid, glycerin, methylparaben, natural and artificial banana flavor, propylene glycol, propylparaben, purified water, sodium acetate (anhydrous), sucralose

Questions?

Call 1-866-923-4914

PRINCIPAL DISPLAY PANEL - 120 mL Bottle Carton

Compareto active ingredient
in Children's Zyrtec®*

NDC 37808-102-08

H-E-B®

Children's

Allergy
Relief

Cetirizine Hydrochloride
Oral Solution 1 mg/mL
Antihistamine / ALLERGY

Indoor & Outdoor Allergies

Ages 2 years and older
Relief of:

- Sneezing • Runny Nose
- Itchy, Watery Eyes
- Itchy Throat or Nose

24
Hour

DYE
FREE

Alcohol Free
Sugar Free

Dosing Cup Enclosed

Grape
Flavor

4 FL OZ (120 mL)